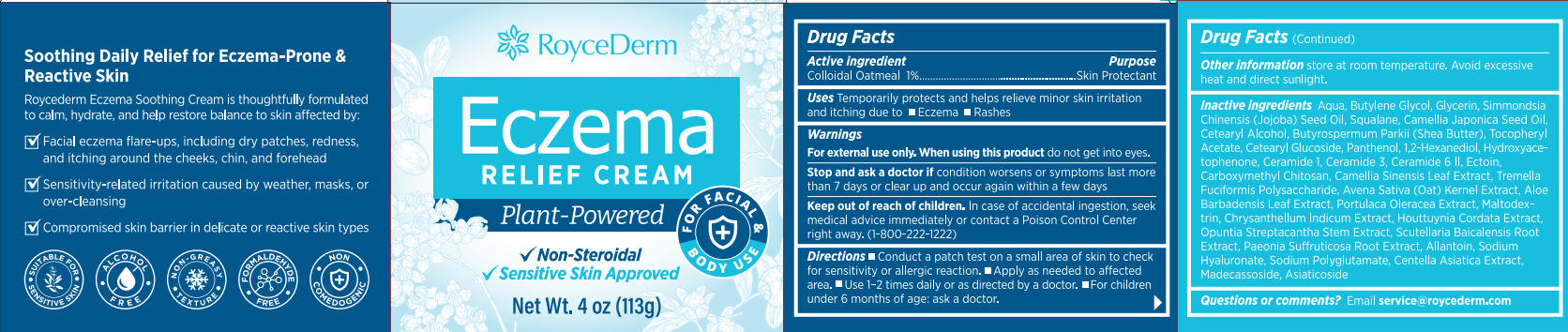 DRUG LABEL: RoyceDerm Eczema Relief Cream
NDC: 85424-010 | Form: CREAM
Manufacturer: RoyceDerm LLC
Category: otc | Type: HUMAN OTC DRUG LABEL
Date: 20250905

ACTIVE INGREDIENTS: OATMEAL 1.13 g/113 g
INACTIVE INGREDIENTS: AQUA; GLYCERIN; BUTYLENE GLYCOL; .ALPHA.-TOCOPHEROL ACETATE, D-; BUTYROSPERMUM PARKII (SHEA) BUTTER; HYDROXYACETOPHENONE; ASIATICOSIDE; ALOE BARBADENSIS LEAF; CHRYSANTHELLUM INDICUM TOP; ECTOIN; MALTODEXTRIN; CETEARYL GLUCOSIDE; PANTHENOL; HOUTTUYNIA CORDATA FLOWERING TOP; CENTELLA ASIATICA TRITERPENOIDS; OAT; N-CARBOXYMETHYLCHITOSAN; CERAMIDE 6 II; PURSLANE; PAEONIA SUFFRUTICOSA ROOT; SODIUM POLYGLUTAMATE (200000 MW); MADECASSOSIDE; CAMELLIA SINENSIS LEAF; SODIUM HYALURONATE; CETEARYL ALCOHOL; SQUALANE; CAMELLIA JAPONICA SEED OIL; SIMMONDSIA CHINENSIS (JOJOBA) SEED OIL; OPUNTIA STREPTACANTHA STEM; 1,2-HEXANEDIOL; CERAMIDE 1; TREMELLA FUCIFORMIS WHOLE; SCUTELLARIA BAICALENSIS ROOT; ALLANTOIN; CERAMIDE 3

Initial Drug Listing - RoyceDerm Eczema Relief Cream

ACTIVE INGREDIENT

Colloidal Oatmeal 1%

PURPOSE

Skin Protectant

DOSAGE AND ADMINISTRATION

Temporarily protects and helps relieve minor skin irritationand itching due to Eczema and Rashes

WARNINGS

For external use only

WHEN USING

do not get into eyes

ASK DOCTOR

condition worsens or symptoms last morethan 7 days or clear up and occur again within a few days

KEEP OUT OF REACH OF CHILDREN

In case of accidental ingestion, seek medical advice immediately or contact a Poison Control Centerright away.(1-800-222-1222)

INDICATIONS AND USAGE

- Conduct a patch test on a small area of skin to checkfor sensitivity or allergic reaction.
- Apply as needed to affectedarea.
- Use 1-2 times daily or as directed by a doctor.
- For childrenunder 6 months of age: ask a doctor.

OTHER SAFETY INFORMATION

store at room temperature. Avoid excessive heat and direct sunlight.

INACTIVE INGREDIENT

Aqua, Butylene Glycol, Glycerin, Simmondsia Chinensis (Jojoba) Seed Oil, Squalane, Camellia Japonica Seed Oil,Cetearyl Alcohol, Butyrospermum Parkii (Shea Butter), Tocopheryl Acetate, Cetearyl Glucoside, Panthenol, 1,2-Hexanediol, Hydroxyacetophenone, Ceramide 1, Ceramide 3, Ceramide 6 ll, Ectoin,Carboxymethyl Chitosan, Camellia Sinensis Leaf Extract, Tremella Fuciformis Polysaccharide, Avena Sativa (Oat) Kernel Extract, Aloe Barbadensis Leaf Extract, Portulaca Oleracea Extract, Maltodex-trin, Chrysanthellum Indicum Extract, Houttuynia Cordata ExtractOpuntia Streptacantha Stem Extract, Scutellaria Baicalensis Root Extract, Paeonia Suffruticosa Root Extract, Allantoin, Sodium Hyaluronate, Sodium Polyglutamate, Centella Asiatica Extract, Madecassoside, Asiaticoside

QUESTIONS

Email service@roycederm.com